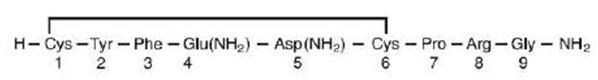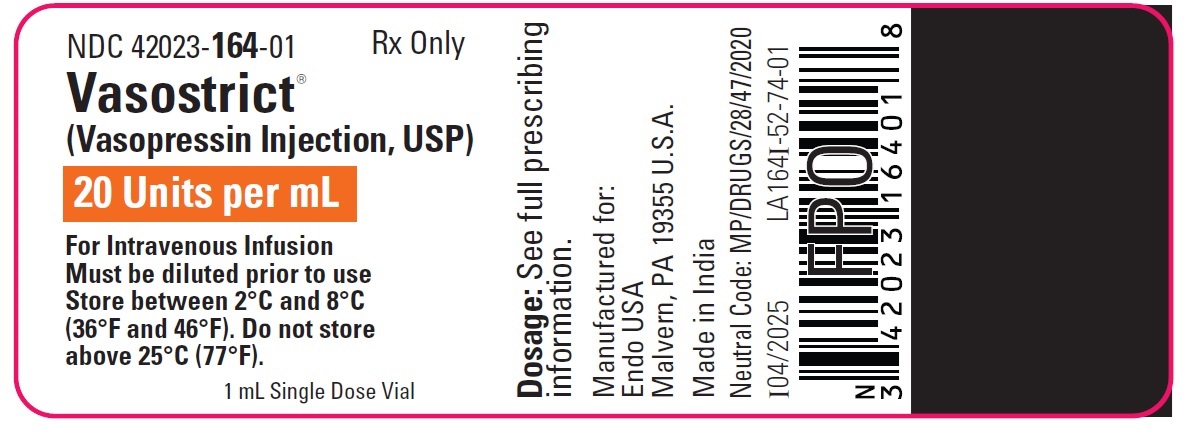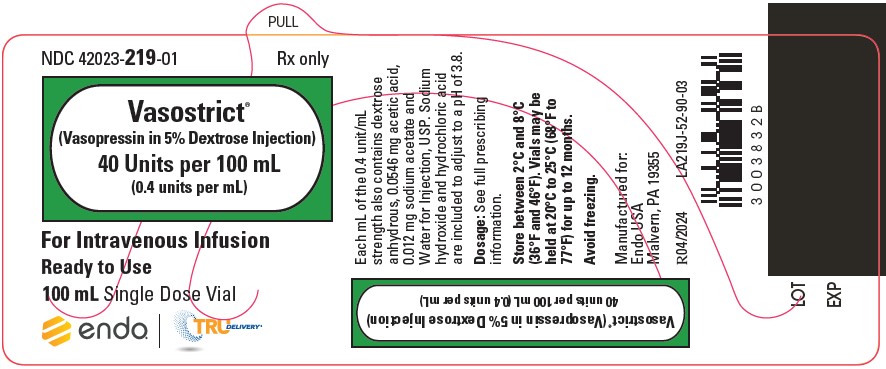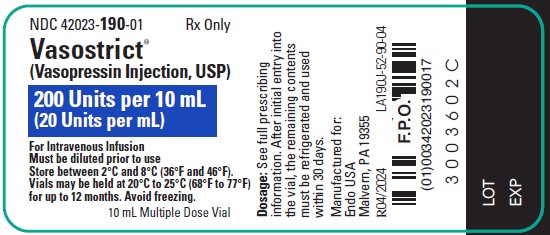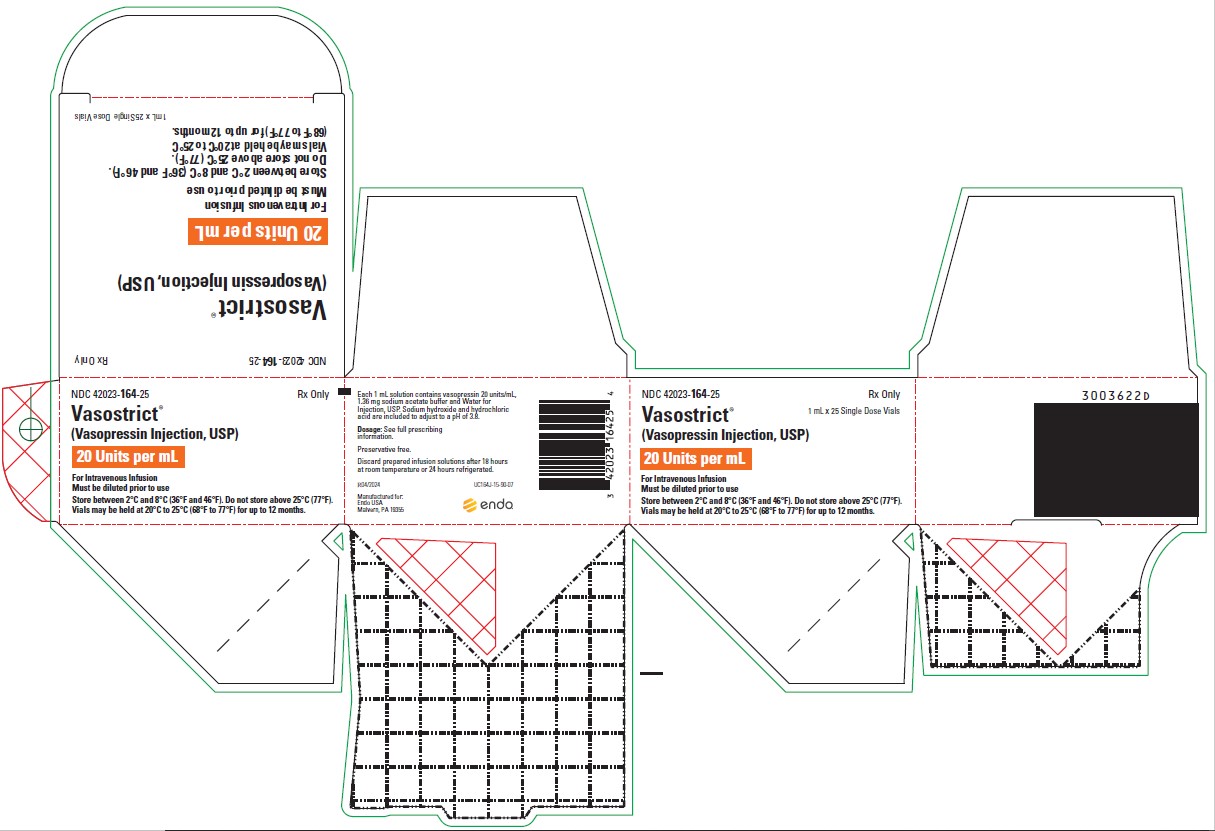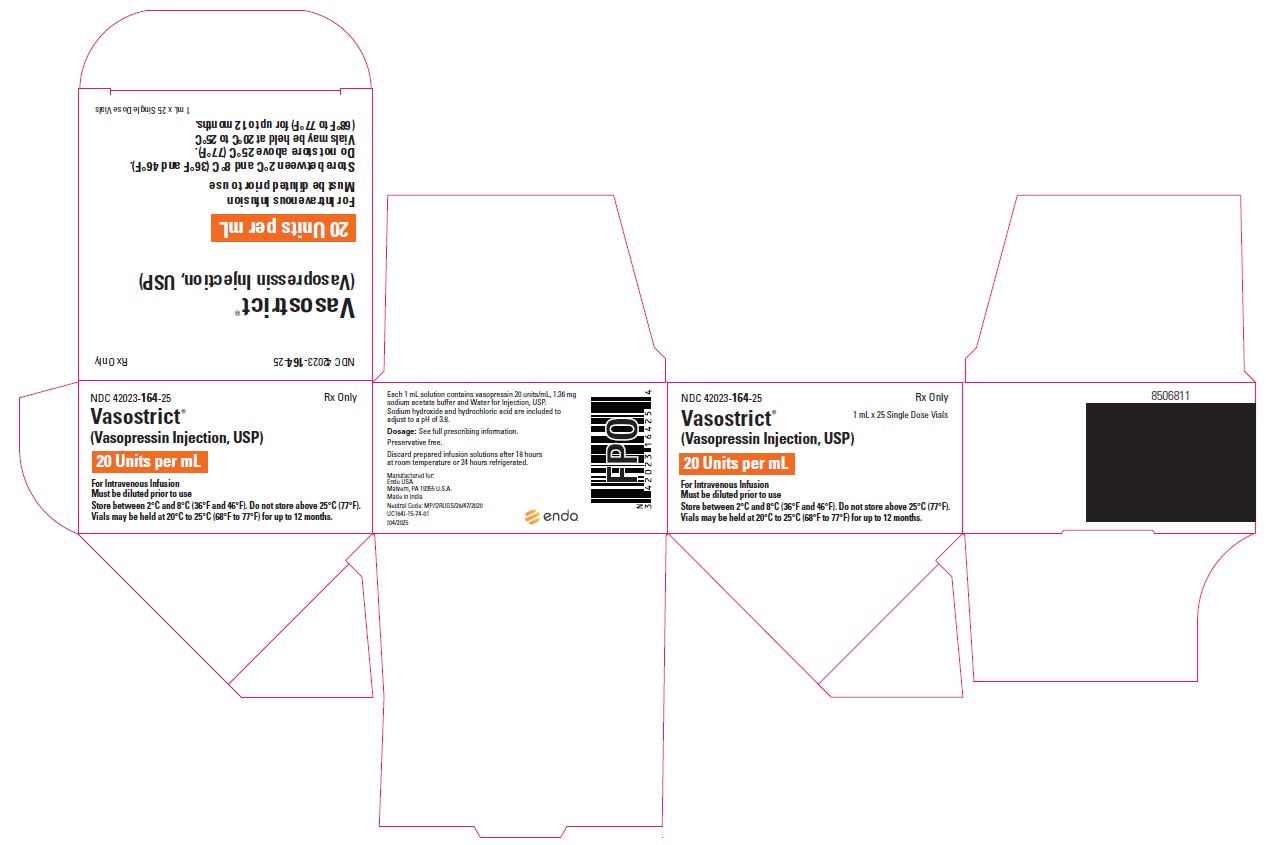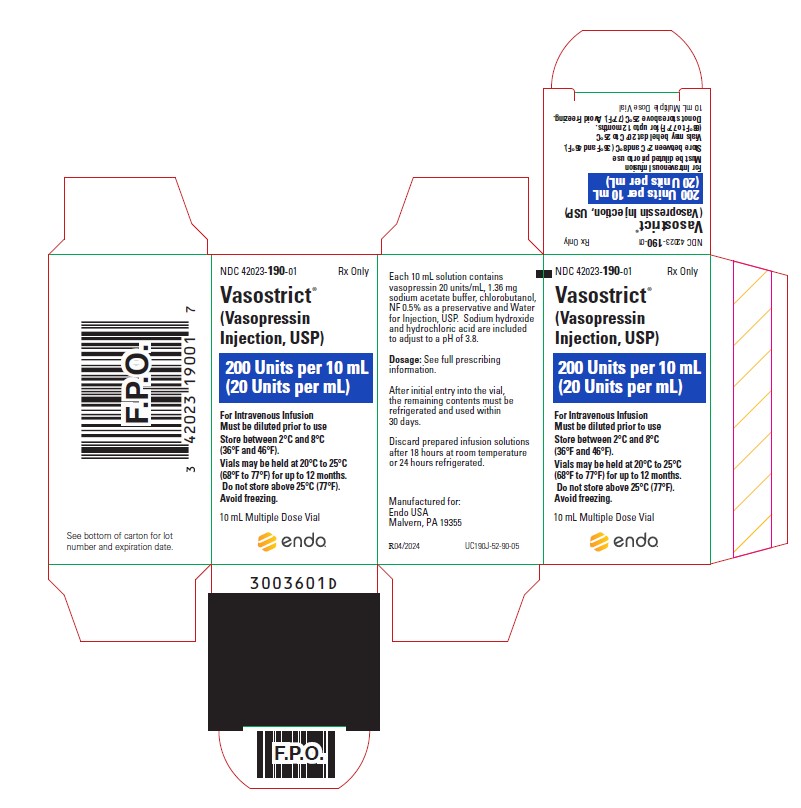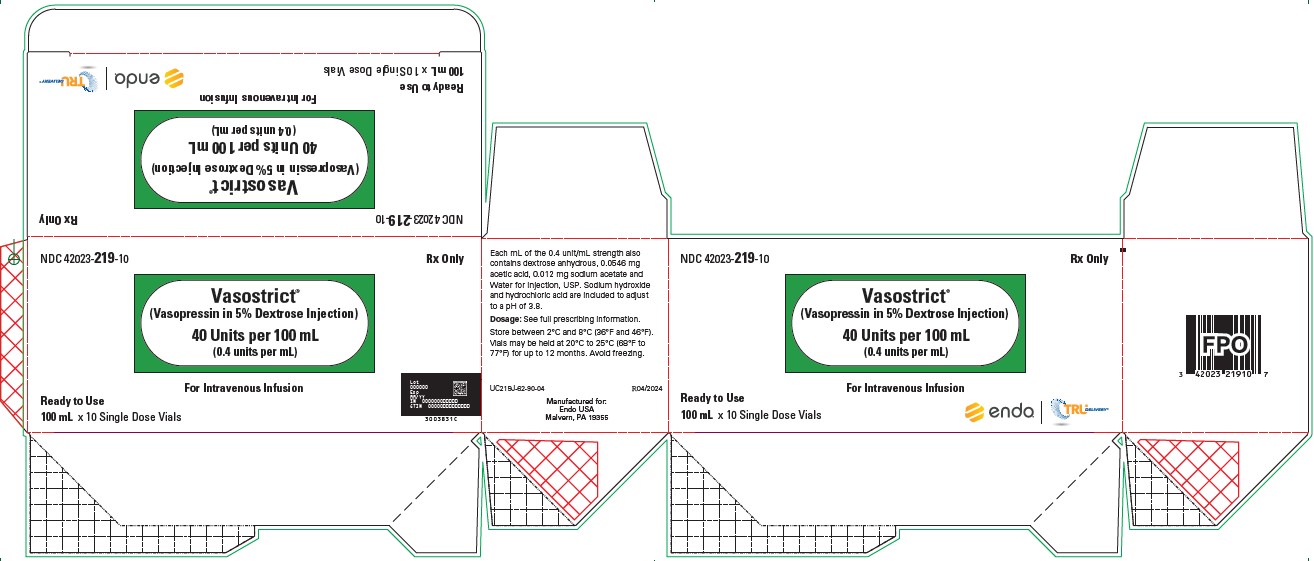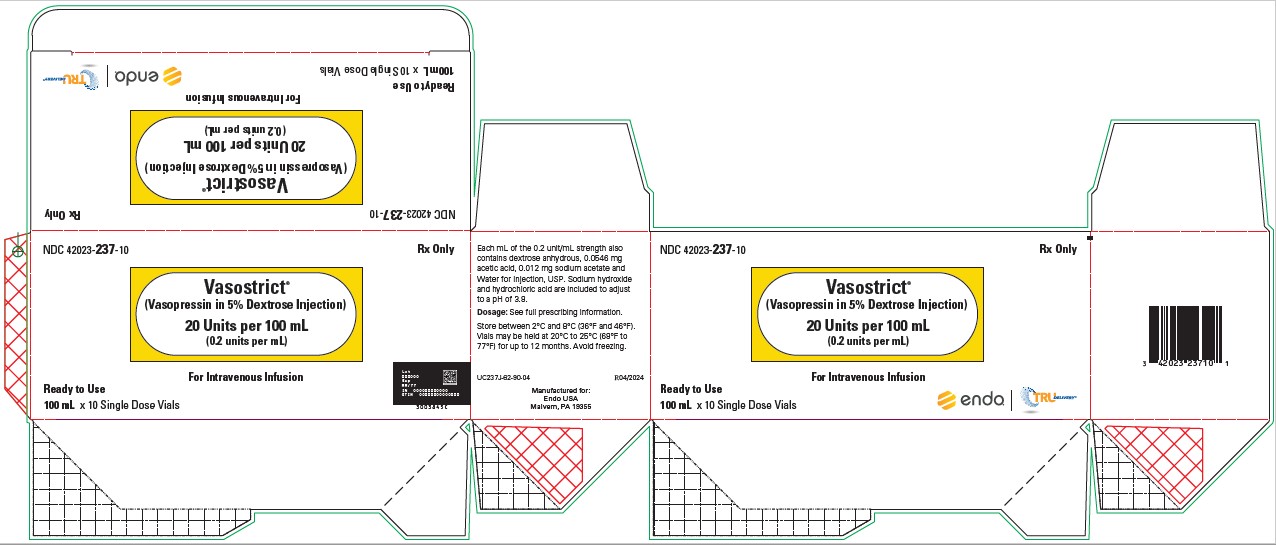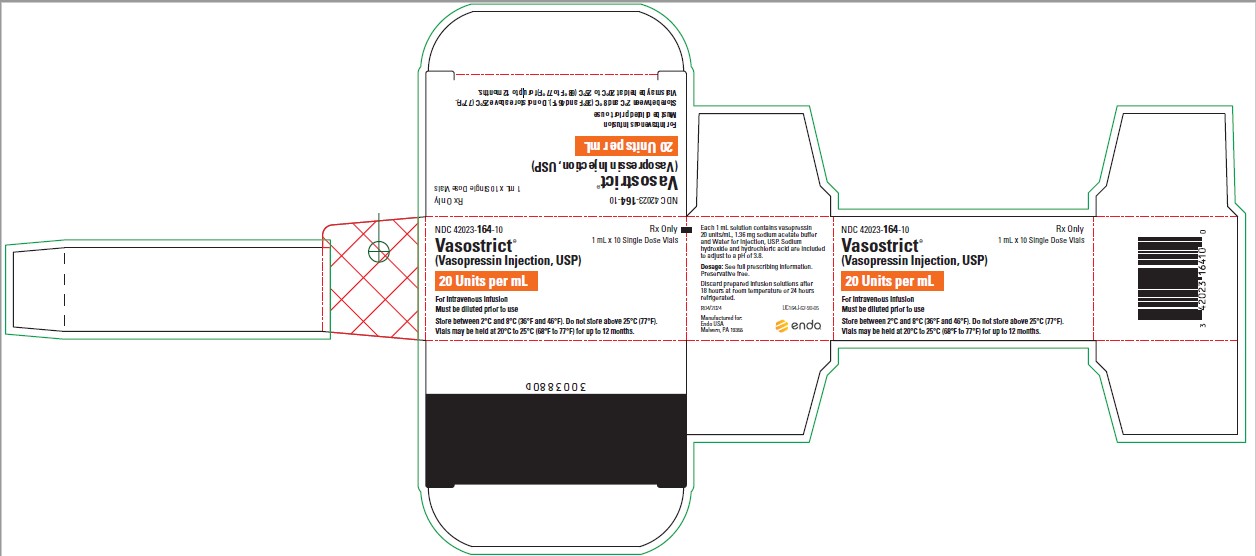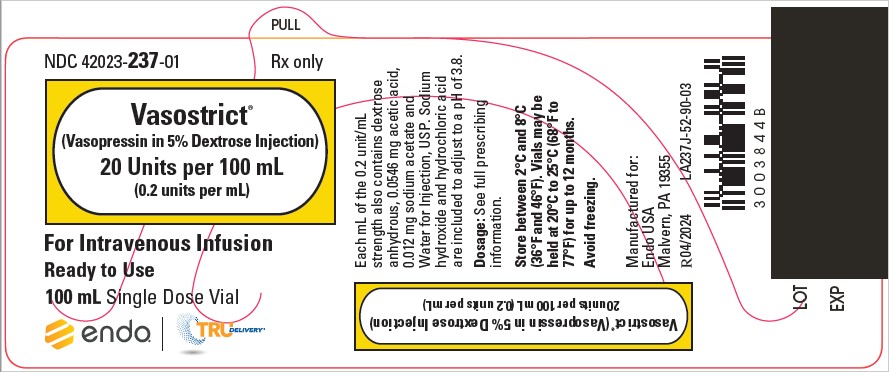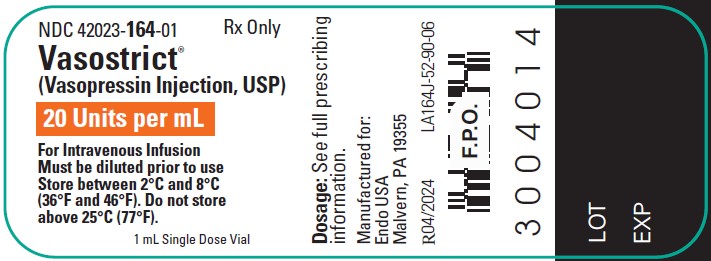 DRUG LABEL: Vasostrict
NDC: 42023-164 | Form: INJECTION
Manufacturer: Par Health USA, LLC
Category: prescription | Type: HUMAN PRESCRIPTION DRUG LABEL
Date: 20250314

ACTIVE INGREDIENTS: VASOPRESSIN, UNSPECIFIED 20 [USP'U]/1 mL
INACTIVE INGREDIENTS: WATER; SODIUM ACETATE 1.36 mg/1 mL; SODIUM HYDROXIDE; HYDROCHLORIC ACID

HIGHLIGHTS OF PRESCRIBING INFORMATION

These highlights do not include all the information needed to use VASOSTRICT® safely and effectively. See full prescribing information for VASOSTRICT®.
VASOSTRICT® (vasopressin injection) for intravenous use
VASOSTRICT® (vasopressin in dextrose injection) for intravenous use
Initial U.S. Approval: 2014

1 INDICATIONS AND USAGE

- Vasostrict® is indicated to increase blood pressure in adults with vasodilatory shock who remain hypotensive despite fluids and catecholamines. (1)

2 DOSAGE AND ADMINISTRATION

- Dilute 20 units/mL single dose vial or 200 units/10 mL (20 units/mL) multiple dose vial contents with normal saline (0.9% sodium chloride) or 5% dextrose in water (D5W) to either 0.1 units/mL or 1 unit/mL for intravenous administration. Discard unused diluted solution after 18 hours at room temperature or 24 hours under refrigeration. (2.1)
- The 20 units/100 mL, 40 units/100 mL, 60 units/100 mL and 50 units/50 mL single dose vials do not require further dilution prior to administration. (2.1)
- Post-cardiotomy shock: 0.03 to 0.1 units/minute (2.2)
- Septic shock: 0.01 to 0.07 units/minute (2.2)

3 DOSAGE FORMS AND STRENGTHS

- Injection:
  - 20 units/mL in a single dose vial. To be used after dilution.
  - 200 units/10 mL (20 units/mL) in a multiple dose vial. To be used after dilution.
  - 20 units/100 mL (0.2 units/mL) premixed in dextrose in a single dose vial. Ready to use.
  - 40 units/100 mL (0.4 units/mL) premixed in dextrose in a single dose vial. Ready to use.
  - 60 units/100 mL (0.6 units/mL) premixed in dextrose in a single dose vial. Ready to use.
  - 50 units/50 mL (1 unit/mL) premixed in dextrose in a single dose vial. Ready to use.

4 CONTRAINDICATIONS

- Vasostrict® 10 mL multiple dose vial is contraindicated in patients with known allergy or hypersensitivity to 8‑L-arginine vasopressin or chlorobutanol. The 1 mL single dose vial, 50 mL and 100 mL pre-mixed single dose vial does not contain chlorobutanol and is therefore contraindicated only in patients with a known allergy or hypersensitivity to 8-L-arginine vasopressin. (4)

5 WARNINGS AND PRECAUTIONS

- Can worsen cardiac function. (5.1)
- Reversible diabetes insipidus (5.2)

6 ADVERSE REACTIONS

The most common adverse reactions include decreased cardiac output, bradycardia, tachyarrhythmias, hyponatremia and ischemia (coronary, mesenteric, skin, digital). (6)

To report SUSPECTED ADVERSE REACTIONS, contact Endo at 1-800-828-9393 or FDA at 1-800-FDA-1088 or www.fda.gov/medwatch.

7 DRUG INTERACTIONS

- Pressor effects of catecholamines and Vasostrict® are expected to be additive. (7.1)
- Indomethacin may prolong effects of Vasostrict®. (7.2)
- Co-administration of ganglionic blockers or drugs causing SIADH may increase the pressor response. (7.3, 7.4)
- Co-administration of drugs causing diabetes insipidus may decrease the pressor response. (7.5)

8 USE IN SPECIFIC POPULATIONS

- Pregnancy: May induce uterine contractions. (8.1)
- Pediatric Use: Safety and effectiveness have not been established. (8.4)
- Geriatric Use: No safety issues have been identified in older patients. (8.5)

FULL PRESCRIBING INFORMATION

1 INDICATIONS AND USAGE

Vasostrict® is indicated to increase blood pressure in adults with vasodilatory shock who remain hypotensive despite fluids and catecholamines.

2 DOSAGE AND ADMINISTRATION

2.1 Preparation of Solution

Inspect parenteral drug products for particulate matter and discoloration prior to use, whenever solution and container permit.

Vasostrict® Solution for Dilution, 20 units/mL and 200 units/10 mL (20 units/mL)

Dilute Vasostrict® in normal saline (0.9% sodium chloride) or 5% dextrose in water (D5W) prior to use for intravenous administration. Discard unused diluted solution after 18 hours at room temperature or 24 hours under refrigeration.

Table 1 Preparation of diluted solutions
Fluid restriction? | Final concentration | Mix
Fluid restriction? | Final concentration | Vasostrict® | Diluent
No | 0.1 units/mL | 2.5 mL (50 units) | 500 mL
Yes | 1 unit/mL | 5 mL (100 units) | 100 mL

Vasostrict® Premixed Solution, 20 units/100 mL (0.2 units/mL), 40 units/100 mL (0.4 units/mL), 60 units/100 mL (0.6 units/mL) and 50 units/50 mL (1 unit/mL)

This product does not require further dilution prior to administration.

2.2 Administration

In general, titrate to the lowest dose compatible with a clinically acceptable response.

The recommended starting dose is:

Post-cardiotomy shock: 0.03 units/minute

Septic Shock: 0.01 units/minute

Titrate up by 0.005 units/minute at 10- to 15-minute intervals until the target blood pressure is reached. There are limited data for doses above 0.1 units/minute for post-cardiotomy shock and 0.07 units/minute for septic shock. Adverse reactions are expected to increase with higher doses.

After target blood pressure has been maintained for 8 hours without the use of catecholamines, taper vasopressin injection by 0.005 units/minute every hour as tolerated to maintain target blood pressure.

3 DOSAGE FORMS AND STRENGTHS

Injection: vasopressin injection, USP is a clear, practically colorless solution available as:

- 20 units/mL in a single dose vial. To be used after dilution.
- 200 units/10 mL (20 units/mL) in a multiple dose vial. To be used after dilution.
- 20 units/100 mL (0.2 units/mL) premixed in dextrose in a single dose vial. Ready to use.
- 40 units/100 mL (0.4 units/mL) premixed in dextrose in a single dose vial. Ready to use.
- 60 units/100 mL (0.6 units/mL) premixed in dextrose in a single dose vial. Ready to use.
- 50 units/50 mL (1 unit/mL) premixed in dextrose in a single dose vial. Ready to use.

4 CONTRAINDICATIONS

Vasostrict® 10 mL multiple dose vial is contraindicated in patients with known allergy or hypersensitivity to 8‑L-arginine vasopressin or chlorobutanol. The 1 mL single dose vial, 50 mL and 100 mL pre-mixed single dose vial does not contain chlorobutanol and is therefore contraindicated only in patients with a known allergy or hypersensitivity to 8-L-arginine vasopressin.

5 WARNINGS AND PRECAUTIONS

5.1 Worsening Cardiac Function

A decrease in cardiac index may be observed with the use of vasopressin.

5.2 Reversible Diabetes Insipidus

Patients may experience reversible diabetes insipidus, manifested by the development of polyuria, a dilute urine, and hypernatremia, after cessation of treatment with vasopressin. Monitor serum electrolytes, fluid status and urine output after vasopressin discontinuation. Some patients may require readministration of vasopressin or administration of desmopressin to correct fluid and electrolyte shifts.

6 ADVERSE REACTIONS

The following adverse reactions associated with the use of vasopressin were identified in the literature. Because these reactions are reported voluntarily from a population of uncertain size, it is not possible to estimate their frequency reliably or to establish a causal relationship to drug exposure.

Bleeding/lymphatic system disorders: Hemorrhagic shock, decreased platelets, intractable bleeding

Cardiac disorders: Right heart failure, atrial fibrillation, bradycardia, myocardial ischemia

Gastrointestinal disorders: Mesenteric ischemia

Hepatobiliary: Increased bilirubin levels

Renal/urinary disorders: Acute renal insufficiency

Vascular disorders: Distal limb ischemia

Metabolic: Hyponatremia

Skin: Ischemic lesions

Postmarketing Experience

Reversible diabetes insipidus [see Warnings and Precautions (5.2)]

7 DRUG INTERACTIONS

7.1 Catecholamines

Use with catecholamines is expected to result in an additive effect on mean arterial blood pressure and other hemodynamic parameters. Hemodynamic monitoring is recommended; adjust the dose of vasopressin as needed.

7.2 Indomethacin

Use with indomethacin may prolong the effect of Vasostrict® on cardiac index and systemic vascular resistance. Hemodynamic monitoring is recommended; adjust the dose of vasopressin as needed [see Clinical Pharmacology (12.3)].

7.3 Ganglionic Blocking Agents

Use with ganglionic blocking agents may increase the effect of Vasostrict® on mean arterial blood pressure. Hemodynamic monitoring is recommended; adjust the dose of vasopressin as needed [see Clinical Pharmacology (12.3)].

7.4 Drugs Suspected of Causing SIADH

Use with drugs suspected of causing SIADH (e.g., SSRIs, tricyclic antidepressants, haloperidol, chlorpropamide, enalapril, methyldopa, pentamidine, vincristine, cyclophosphamide, ifosfamide, felbamate) may increase the pressor effect in addition to the antidiuretic effect of Vasostrict®. Hemodynamic monitoring is recommended; adjust the dose of vasopressin as needed.

7.5 Drugs Suspected of Causing Diabetes Insipidus

Use with drugs suspected of causing diabetes insipidus (e.g., demeclocycline, lithium, foscarnet, clozapine) may decrease the pressor effect in addition to the antidiuretic effect of Vasostrict®. Hemodynamic monitoring is recommended; adjust the dose of vasopressin as needed.

8 USE IN SPECIFIC POPULATIONS

8.1 Pregnancy

Risk Summary

There are no available data on Vasostrict® use in pregnant women to inform a drug associated risk of major birth defects, miscarriage, or adverse maternal or fetal outcomes. Animal reproduction studies have not been conducted with vasopressin.

Clinical Considerations

Dose adjustments during pregnancy and the postpartum period: Because of increased clearance of vasopressin in the second and third trimester, the dose of Vasostrict® may need to be increased [see Dosage and Administration (2.2) and Clinical Pharmacology (12.3)].

Maternal adverse reactions: Vasostrict® may produce tonic uterine contractions that could threaten the continuation of pregnancy.

8.2 Lactation

There are no data on the presence of vasopressin injection in either human or animal milk, the effects on the breastfed infant, or the effects on milk production.

8.4 Pediatric Use

Safety and effectiveness of Vasostrict® in pediatric patients with vasodilatory shock have not been established.

8.5 Geriatric Use

Clinical studies of vasopressin did not include sufficient numbers of subjects aged 65 and over to determine whether they respond differently from younger subjects. Other reported clinical experience has not identified differences in responses between the elderly and younger patients. In general, dose selection for an elderly patient should be cautious, usually starting at the low end of the dosing range, reflecting the greater frequency of decreased hepatic, renal, or cardiac function, and of concomitant disease or other drug therapy [see Warnings and Precautions (5), Adverse Reactions (6), and Clinical Pharmacology (12.3)].

10 OVERDOSAGE

Overdosage with Vasostrict® can be expected to manifest as consequences of vasoconstriction of various vascular beds (peripheral, mesenteric, and coronary) and as hyponatremia. In addition, overdosage may lead less commonly to ventricular tachyarrhythmias (including Torsade de Pointes), rhabdomyolysis, and non-specific gastrointestinal symptoms.

Direct effects will resolve within minutes of withdrawal of treatment.

11 DESCRIPTION

Vasopressin is a polypeptide hormone. Vasostrict® is a sterile, aqueous solution of synthetic arginine vasopressin for intravenous administration.

The 1 mL solution contains vasopressin 20 units/mL, 1.36 mg sodium acetate buffer and Water for Injection, USP. The 10 mL solution contains vasopressin 20 units/mL, 1.36 mg sodium acetate buffer, chlorobutanol, NF 0.5% as a preservative and Water for Injection, USP. Sodium hydroxide and hydrochloric acid are included to adjust to a pH of 3.8.

The 50 mL solution contains vasopressin 1 unit/mL. Each mL of the 1 unit/mL strength also contains dextrose anhydrous, 0.0546 mg acetic acid, 0.012 mg sodium acetate and Water for Injection, USP. Sodium hydroxide and hydrochloric acid are included to adjust to a pH of 3.8.

The 100 mL solution contains vasopressin 0.2 units/mL, 0.4 units/mL, or 0.6 units/mL. Each mL of the 0.2 unit/mL strength also contains dextrose anhydrous, 0.0546 mg acetic acid, 0.012 mg sodium acetate and Water for Injection, USP. Each mL of the 0.4 unit/mL strength also contains dextrose anhydrous, 0.0546 mg acetic acid, 0.012 mg sodium acetate and Water for Injection, USP. Each mL of the 0.6 unit/mL strength also contains dextrose anhydrous, 0.0546 mg acetic acid, 0.012 mg sodium acetate and Water for Injection, USP. Sodium hydroxide and hydrochloric acid are included to adjust to a pH of 3.8.

Each vial of the Vasostrict® premixed solutions contains 5% Dextrose in approximately 100 mL Water for Injection. The chemical name of vasopressin is Cyclo (1-6) L-Cysteinyl-L-Tyrosyl-L-Phenylalanyl-L-Glutaminyl-L-Asparaginyl-L-Cysteinyl-L-Prolyl-L-Arginyl-L-Glycinamide. It is a white to off-white amorphous powder, freely soluble in water. The structural formula is:

Molecular Formula: C46H65N15O12S2 Molecular Weight: 1084.23

One mg is equivalent to 530 units.

12 CLINICAL PHARMACOLOGY

12.1 Mechanism of Action

Vasopressin causes vasoconstriction by binding to V1 receptors on vascular smooth muscle coupled to the Gq/11-phospholipase C-phosphatidyl-inositol-triphosphate pathway, resulting in the release of intracellular calcium. In addition, vasopressin stimulates antidiuresis via stimulation of V2 receptors which are coupled to adenyl cyclase.

12.2 Pharmacodynamics

At therapeutic doses exogenous vasopressin elicits a vasoconstrictive effect in most vascular beds including the splanchnic, renal and cutaneous circulation. In addition, vasopressin at pressor doses triggers contractions of smooth muscles in the gastrointestinal tract mediated by muscular V1-receptors and release of prolactin and ACTH via V3 receptors. At lower concentrations typical for the antidiuretic hormone vasopressin inhibits water diuresis via renal V2 receptors. In addition, vasopressin has been demonstrated to cause vasodilation in numerous vascular beds that are mediated by V2, V3, oxytocin and purinergic P2 receptors.

In patients with vasodilatory shock vasopressin in therapeutic doses increases systemic vascular resistance and mean arterial blood pressure and reduces the dose requirements for norepinephrine. Vasopressin tends to decrease heart rate and cardiac output. The pressor effect is proportional to the infusion rate of exogenous vasopressin. The pressor effect reaches its peak within 15 minutes. After stopping the infusion the pressor effect fades within 20 minutes. There is no evidence for tachyphylaxis or tolerance to the pressor effect of vasopressin in patients.

12.3 Pharmacokinetics

Vasopressin plasma concentrations increase linearly with increasing infusion rates from 10 to 200 μU/kg/min. Steady state plasma concentrations are achieved after 30 minutes of continuous intravenous infusion.

Distribution Vasopressin does not appear to bind plasma protein. The volume of distribution is 140 mL/kg.

Elimination

At infusion rates used in vasodilatory shock (0.01 to 0.1 units/minute), the clearance of vasopressin is 9 to 25 mL/min/kg in patients with vasodilatory shock. The apparent t1/2 of vasopressin at these levels is ≤10 minutes.

Metabolism

Serine protease, carboxipeptidase and disulfide oxido-reductase cleave vasopressin at sites relevant for the pharmacological activity of the hormone. Thus, the generated metabolites are not expected to retain important pharmacological activity.

Excretion

Vasopressin is predominantly metabolized and only about 6% of the dose is excreted unchanged into urine.

Specific Populations

Pregnancy: Because of a spillover into blood of placental vasopressinase, the clearance of exogenous and endogenous vasopressin increases gradually over the course of a pregnancy. During the first trimester of pregnancy, the clearance is only slightly increased. However, by the third trimester the clearance of vasopressin is increased about 4-fold and at term up to 5-fold. After delivery, the clearance of vasopressin returns to preconception baseline within two weeks.

Drug Interactions Indomethacin more than doubles the time to offset for vasopressin’s effect on peripheral vascular resistance and cardiac output in healthy subjects [see Drug Interactions (7.2)].

The ganglionic blocking agent tetra-ethylammonium increases the pressor effect of vasopressin by 20% in healthy subjects [see Drug Interactions (7.3)].

Halothane, morphine, fentanyl, alfentanyl and sufentanyl do not impact exposure to endogenous vasopressin.

13 NONCLINICAL TOXICOLOGY

13.1 Carcinogenesis, Mutagenesis, Impairment of Fertility

No formal carcinogenicity or fertility studies with vasopressin have been conducted in animals. Vasopressin was found to be negative in the in vitro bacterial mutagenicity (Ames) test and the in vitro Chinese hamster ovary (CHO) cell chromosome aberration test. In mice, vasopressin has been reported to have an effect on function and fertilizing ability of spermatozoa.

13.2 Animal Toxicology and/or Pharmacology

No toxicology studies were conducted with vasopressin.

14 CLINICAL STUDIES

Increases in systolic and mean blood pressure following administration of vasopressin were observed in 7 studies in septic shock and 8 in post-cardiotomy vasodilatory shock.

16 HOW SUPPLIED/STORAGE AND HANDLING

Vasostrict® (vasopressin injection, USP) is a clear, practically colorless solution for intravenous administration available as:

NDC 42023-164-10: A carton of 10 single dose vials. Each vial contains vasopressin 1 mL at 20 units/mL.

NDC 42023-164-25: A carton of 25 single dose vials. Each vial contains vasopressin 1 mL at 20 units/mL.

NDC 42023-190-01: A carton of 1 multiple dose vial. Each vial contains vasopressin 10 mL at 200 units/10 mL (20 units/mL).

NDC 42023-219-10: A carton of 10 single dose vials. Each vial contains vasopressin premixed in dextrose 100 mL at 40 units/100 mL (0.4 units/mL).

NDC 42023-220-10: A carton of 10 single dose vials. Each vial contains vasopressin premixed in dextrose 100 mL at 60 units/100 mL (0.6 units/mL).

NDC 42023-237-10: A carton of 10 single dose vials. Each vial contains vasopressin premixed in dextrose 100 mL at 20 units/100 mL (0.2 units/mL).

NDC 42023-268-10: A carton of 10 single dose vials. Each vial contains vasopressin premixed in dextrose 50 mL at 50 units/50 mL (1 unit/mL).

STORAGE AND HANDLING

Store between 2°C and 8°C (36°F and 46°F). Do not freeze.

Vials may be held up to 12 months upon removal from refrigeration to room temperature storage conditions (20°C to 25°C [68°F to 77°F], USP Controlled Room Temperature), anytime within the labeled shelf life. Once removed from refrigeration, unopened vial should be marked to indicate the revised 12 month expiration date. If the manufacturer’s original expiration date is shorter than the revised expiration date, then the shorter date must be used. Do not use Vasostrict® beyond the manufacturer’s expiration date stamped on the vial.

After initial entry into the 10 mL vial, the remaining contents must be refrigerated. Discard the refrigerated 10 mL vial after 30 days after first puncture.

The storage conditions and expiration periods are summarized in the following table.

 | Unopened Refrigerated; 2°C to 8°C (36°F to 46°F) | Unopened Room Temperature; 20°C to 25°C (68°F to 77°F); Do not store above 25°C (77°F) | Opened (After First Puncture)
1 mL Vial | Until manufacturer expiration date | 12 months or until manufacturer expiration date, whichever is earlier | N/A
10 mL Vial | Until manufacturer expiration date | 12 months or until manufacturer expiration date, whichever is earlier | 30 days
50 mL Vial | Until manufacturer expiration date | 12 months or until manufacturer expiration date, whichever is earlier | N/A
100 mL Vial | Until manufacturer expiration date | 12 months or until manufacturer expiration date, whichever is earlier | N/A

Manufactured for:

Endo USA

Malvern, PA 19355 U.S.A.

© 2025 Endo, Inc. or one of its affiliates.

OS164I-01-74-01

Issued: 03/2025